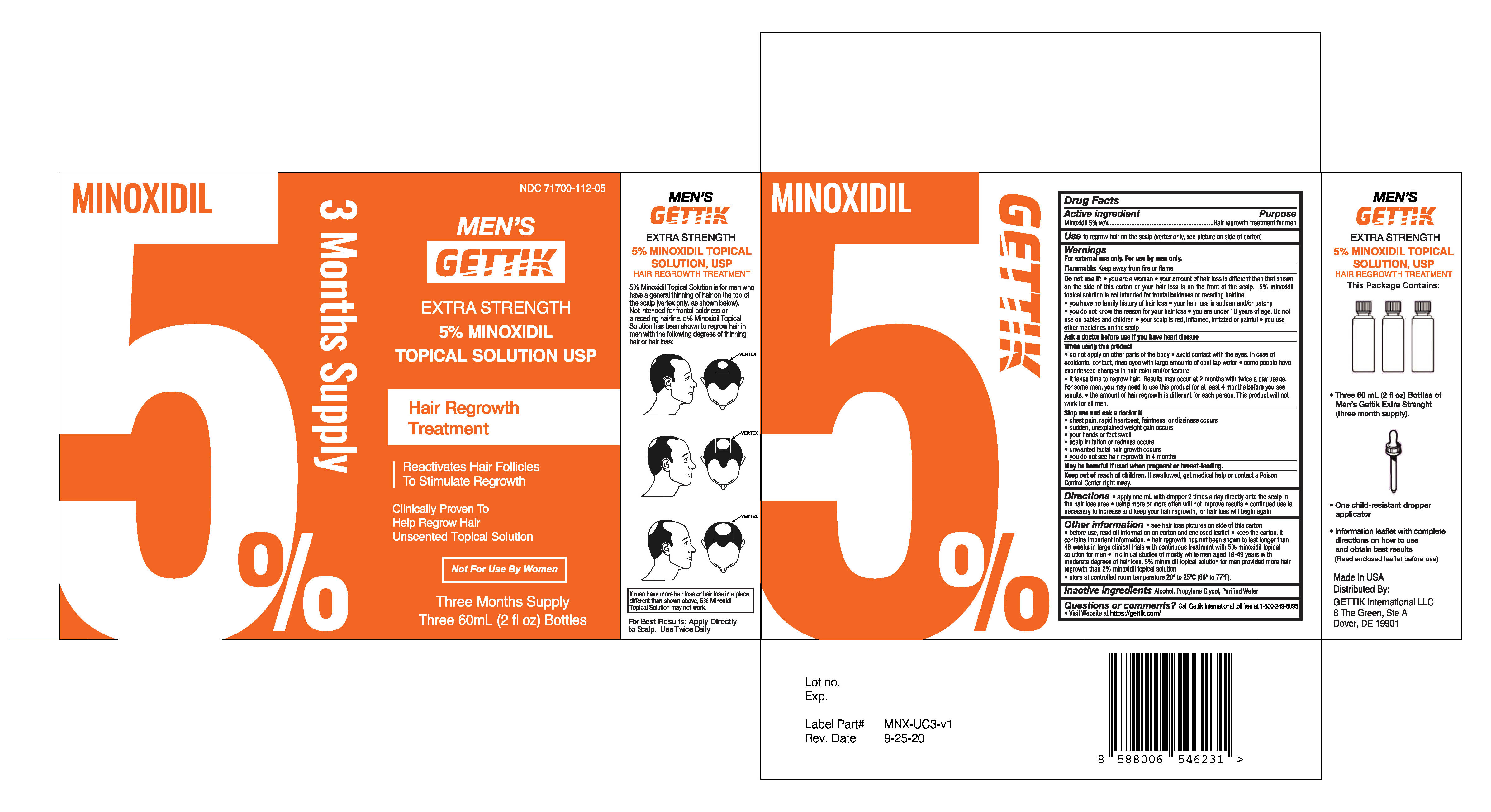 DRUG LABEL: GETTIK Hair Regrowth Treatment
NDC: 71700-112 | Form: LIQUID
Manufacturer: GETTIK International LLC
Category: otc | Type: HUMAN OTC DRUG LABEL
Date: 20241211

ACTIVE INGREDIENTS: MINOXIDIL 50 mg/1 mL
INACTIVE INGREDIENTS: WATER; ALCOHOL; PROPYLENE GLYCOL

ACTIVE INGREDIENT

Minoxidil 5.0% w/v

PURPOSE

Hair regrowth treatment for men

INDICATIONS AND USAGE

To regrow hair on the top of the scalp (vertex only, see pictures on side of carton)

WARNINGS

For external use only

For use by men only

Flammable: Keep away from fire or flame

Do not use if

- you are a woman
- your amount of hair loss is different than that shown on the side of this carton or your hair loss is on the front of the scalp. Minoxidil Topical Solution, 5% is not intended for frontal baldness or receding hairline.
- you have no family history of hair loss
- your hair loss is sudden and/or patchy
- you do not know the reason for your hair loss
- you are under 18 years of age. Do not use on babies and children.
- your scalp is red, inflamed, infected, irritated, or painful
- you use other medicines on the scalp

Ask a doctor before use if you have heart disease

When using this product

- do not apply on other parts of the body
- avoid contact with the eyes. In case of accidental contact, rinse eyes with large amounts of cool tap water.
- some people have experienced changes in hair color and/or texture
- it takes time to regrow hair. Results may occur at 2 months with twice a day usage. For some men, you may need to use this product for at least 4 months before you see results.
- the amount of hair regrowth is different for each person. This product will not work for all men.

Stop use and ask a doctor if

- chest pain, rapid heartbeat, faintness, or dizziness occurs
- sudden, unexplained weight gain occurs
- your hands or feet swell
- scalp irritation or redness occurs
- unwanted facial hair growth occurs
- you do not see hair regrowth in 4 months

May be harmful if used when pregnant or breast-feeding

Keep out of reach of children.

If swallowed, get medical help or contact a Poison Control Center right away.

DOSAGE AND ADMINISTRATION

- apply one ML 2 times a day directly onto the scalp in the hair loss area
- using more or more often will not improve results
- continued use is necessary or hair loss will begin again

OTHER SAFETY INFORMATION

- see hair loss pictures on side of this carton
- before use read all information on carton and enclosed leaflet
- keep the carton, it contains important information
- hair growth has not been shown to last longer than 48 weeks in large clinical trials with continuous treatment with Minoxidil Topical Solution 5%
- in clinical studies with mostly white men aged 18-49 years with moderate degrees of hair loss, Minoxidil Topical Solution 5% provided more hair regrowth than Minoxidil Topical Solutions 2%
- store at controlled room temperature 20 degree to 25 degree C (68 degree to 77 degree F)

INACTIVE INGREDIENT

alcohol 30% v/v, propylene glycol 50% v/v, purified water

QUESTIONS

Questions: Call your health care professional or Gettik at 1-800-249-8095 or visit our website at https://gettik.com